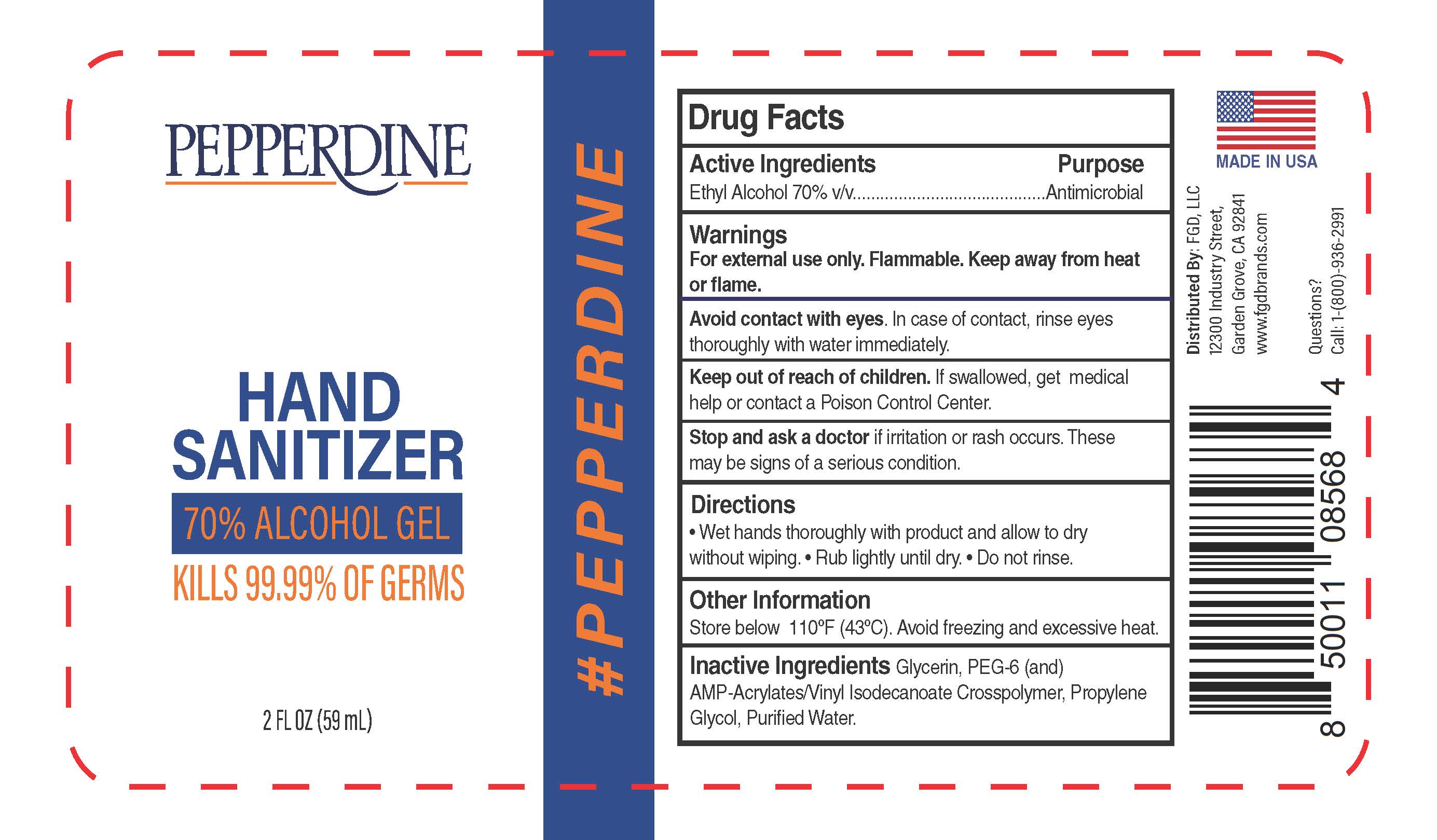 DRUG LABEL: Pepperdine Hand Sanitizer
NDC: 73787-129 | Form: GEL
Manufacturer: FGD, LLC
Category: otc | Type: HUMAN OTC DRUG LABEL
Date: 20210106

ACTIVE INGREDIENTS: ALCOHOL 70 mL/100 mL
INACTIVE INGREDIENTS: ACRYLATES/VINYL ISODECANOATE CROSSPOLYMER (10000 MPA.S NEUTRALIZED AT 0.5%); WATER; PROPYLENE GLYCOL; GLYCERIN; POLYETHYLENE GLYCOL 300

Pepperdine Hand Sanitizer 2 oz.

Active ingredient

Ethyl Alcohol 70%

PURPOSE

Antimicrobial

Uses

Hand Sanitizer to help reduce bacteria that potentially can cause disease. For use when soap and water are not available.

Warnings

For external use only. Highly flammable liquid and vapor.

Causes serious eye irritation. Keep away from heat or flame.

DO NOT USE

- if you are allergic to any of the ingredients
- in children less than 2 months of age
- on open skin wounds

WHEN USING

avoid contact with eyes, ears and mouth. In case of contact with eyes, rinse eyes thoroughly with water.

STOP USE

if irritation or rash occurs. These may be signs of a serious condition.

KEEP OUT OF REACH OF CHILDREN

If swallowed, get medical help or contact a Poison Control Center (1-800-222-1222) right away.

Directions

- Take appropriate amount onto your hand and spread it all the way to fingertips. Rub hands together until dry.
- Supervise Children under 6 years of age when using this product to avoid swallowing.

OTHER SAFETY INFORMATION

- Store between 15-30oC (59-86oF)
- Avoid freezing and excessive heat 40oC (104oF)

Inactive ingredients

Glycerin, PEG-6 (and) AMP-Acrylate/vinyl-Isodecanoate Crosspolymer, Propylene-glycol, Purified Water